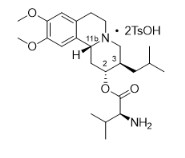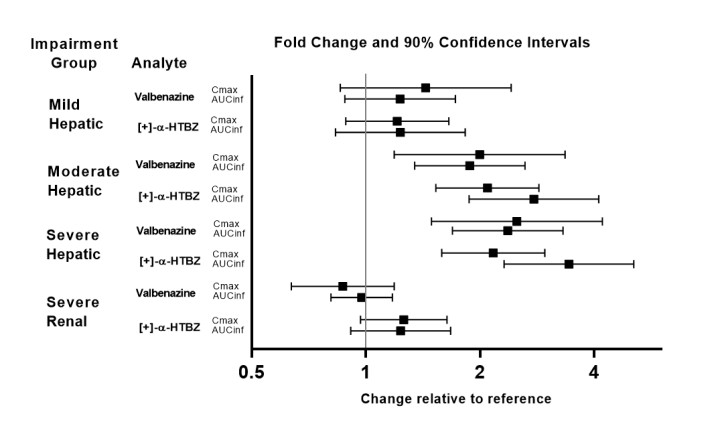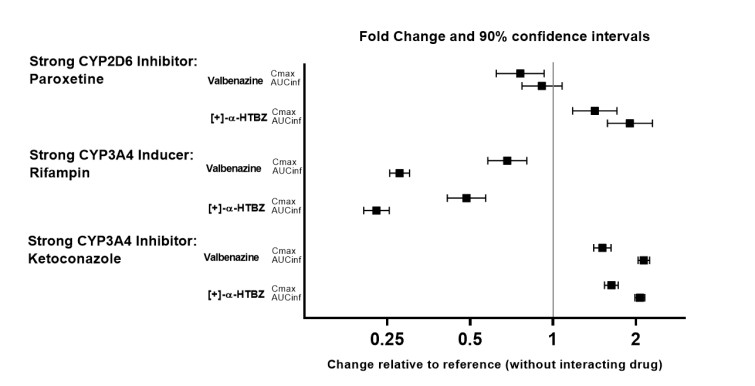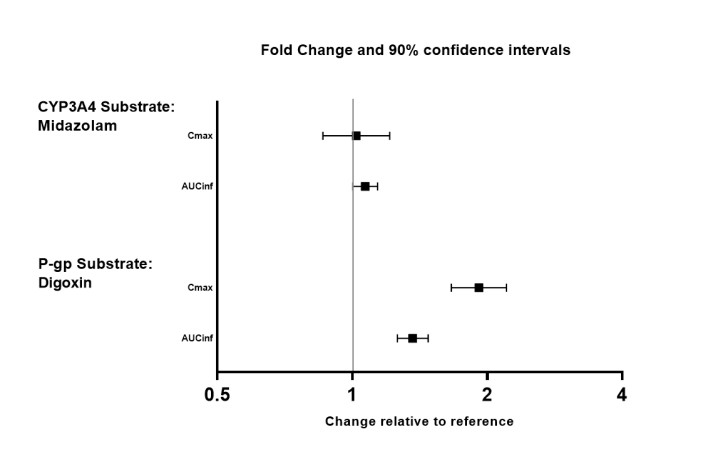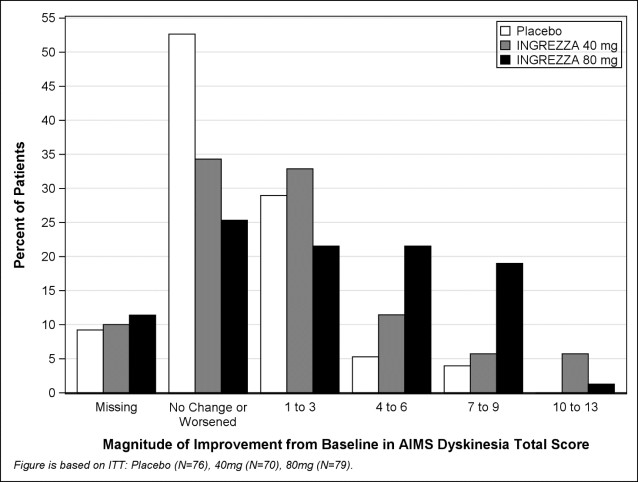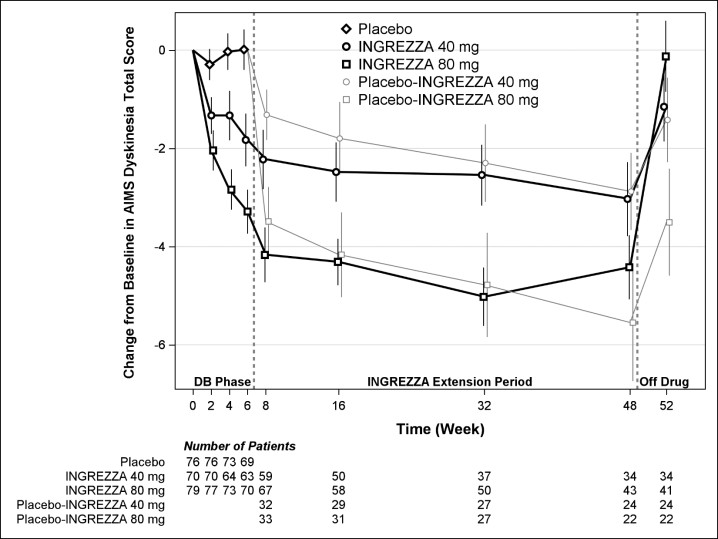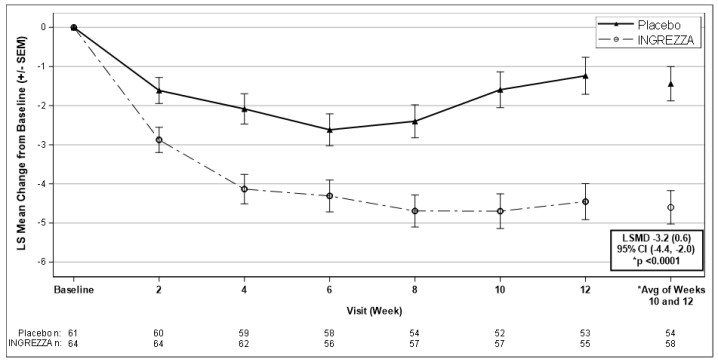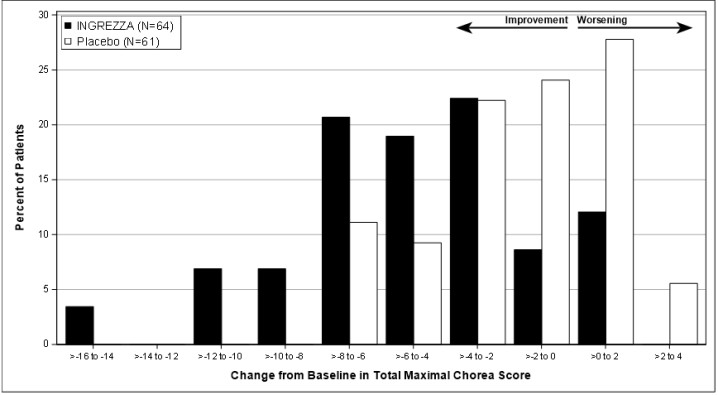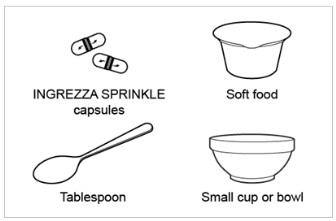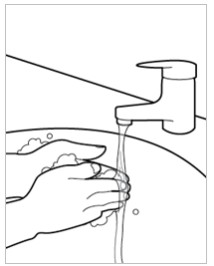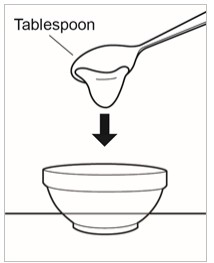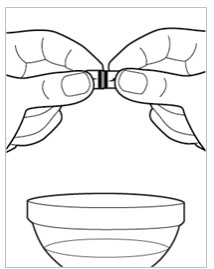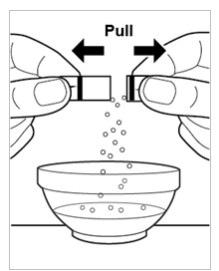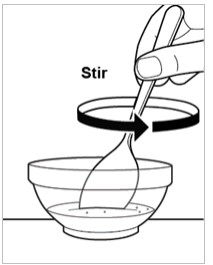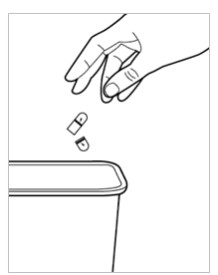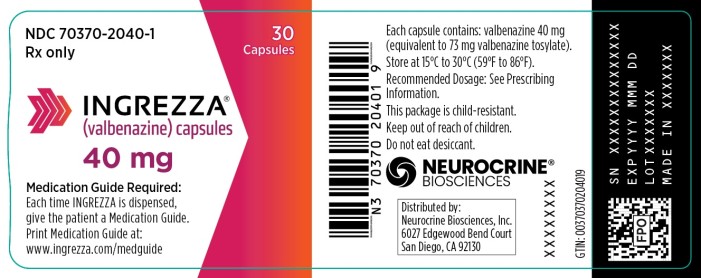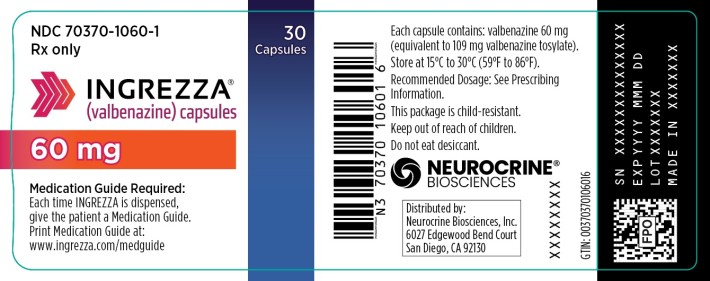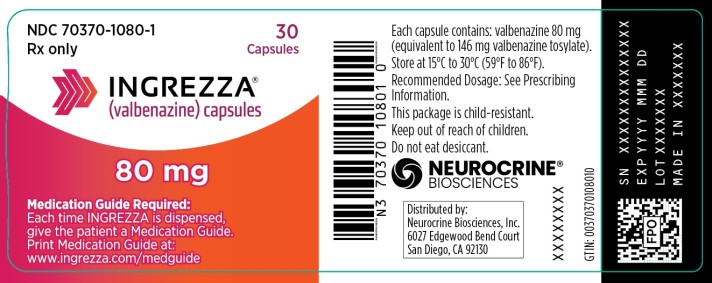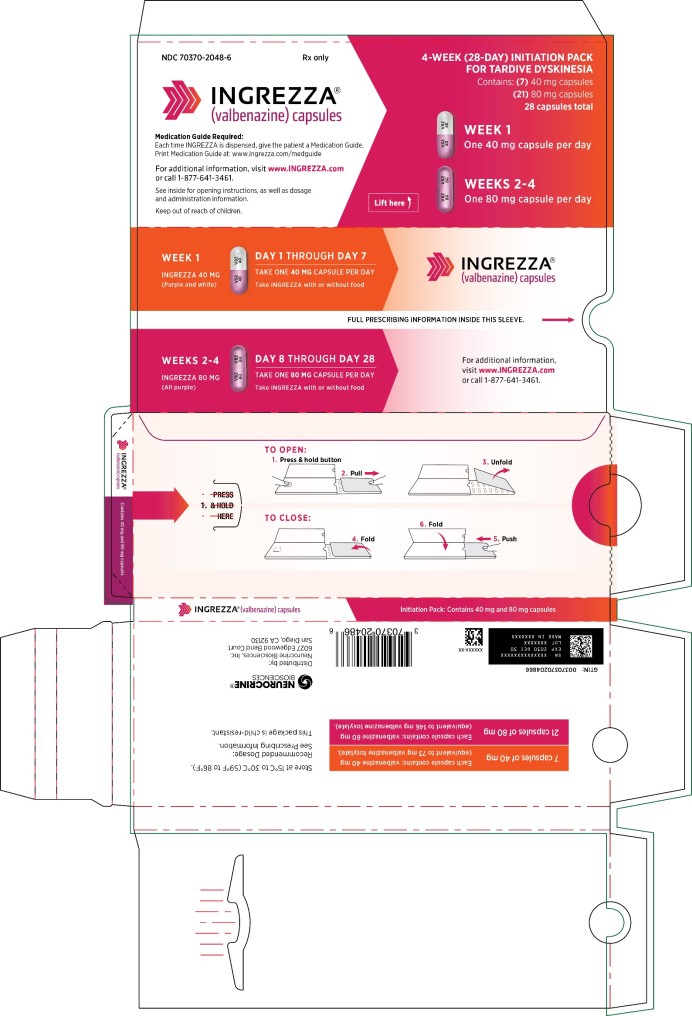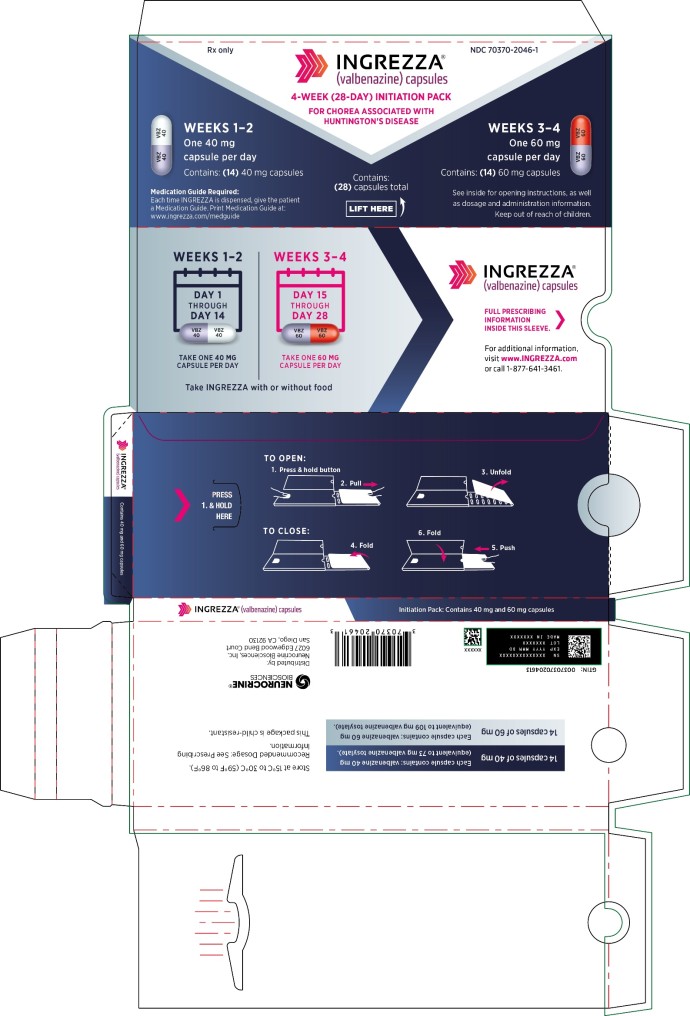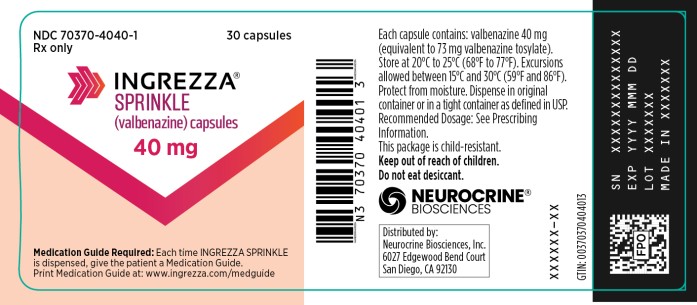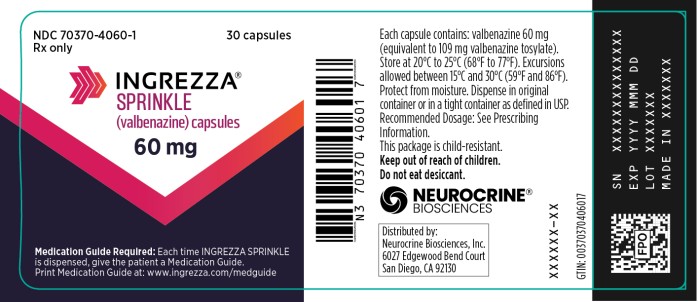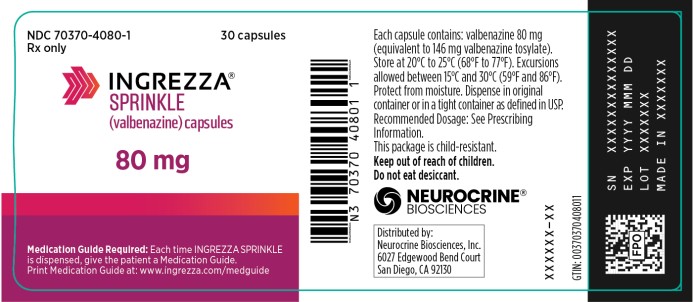 DRUG LABEL: INGREZZA
NDC: 70370-2040 | Form: CAPSULE
Manufacturer: Neurocrine Biosciences, Inc.
Category: prescription | Type: HUMAN PRESCRIPTION DRUG LABEL
Date: 20251001

ACTIVE INGREDIENTS: VALBENAZINE TOSYLATE 40 mg/1 1
INACTIVE INGREDIENTS: GELATIN; FD&C RED NO. 40; FD&C BLUE NO. 1; HYPROMELLOSE, UNSPECIFIED; ISOMALT; MAGNESIUM STEARATE; STARCH, CORN; MICROCRYSTALLINE CELLULOSE

HIGHLIGHTS OF PRESCRIBING INFORMATION

These highlights do not include all the information needed to use INGREZZA or INGREZZA SPRINKLE safely and effectively. See full prescribing information for INGREZZA.
INGREZZA® (valbenazine) capsules, for oral use
INGREZZA® SPRINKLE (valbenazine) capsules, for oral use
Initial U.S. Approval: 2017

WARNING: DEPRESSION AND SUICIDAL IDEATION AND BEHAVIOR IN PATIENTS WITH HUNTINGTON’S DISEASE

See full prescribing information for complete boxed warning.

• Increases the risk of depression and suicidal thoughts and behavior in patients with Huntington’s disease (5.1)

• Balance risks of depression, and suicidal ideation and behavior with the clinical need for treatment of chorea when considering the use of INGREZZA or INGREZZA SPRINKLE (5.1)

• Monitor patients for the emergence or worsening of depression, suicidal ideation, or unusual changes in behavior (5.1)

• Inform patients, caregivers, and families of the risk of depression and suicidal ideation and behavior and instruct them to report behaviors of concern promptly to the treating physician (5.1)

• Exercise caution when treating patients with a history of depression or prior suicide attempts or ideation (5.1)

1 INDICATIONS AND USAGE

INGREZZA and INGREZZA SPRINKLE are vesicular monoamine transporter 2 (VMAT2) inhibitors indicated for the treatment of adults with:
- tardive dyskinesia. (1)
- chorea associated with Huntington’s disease. (1)

2 DOSAGE AND ADMINISTRATION

- Tardive dyskinesia: The initial dosage is 40 mg once daily. After one week, increase the dose to the recommended dosage of 80 mg once daily. (2.1)
- Chorea associated with Huntington’s disease: The initial dosage is 40 mg once daily. Increase the dose in 20 mg increments every two weeks to the recommended dosage of 80 mg once daily. (2.1)
- 40 mg or 60 mg once daily may be considered depending on response and tolerability. (2.1)
- Can be taken with or without food. (2.2)
- INGREZZA SPRINKLE may be opened and sprinkled over soft food (do not use milk or drinking water). INGREZZA SPRINKLE may be swallowed whole with water. Do not crush or chew. (2.2)
- The recommended dosage for patients with moderate or severe hepatic impairment is 40 mg once daily. (2.3)
- The recommended dosage for known CYP2D6 poor metabolizers is 40 mg once daily. (2.4)

3 DOSAGE FORMS AND STRENGTHS

INGREZZA capsules: 40 mg, 60 mg and 80 mg. (3)

INGREZZA SPRINKLE capsules: 40 mg, 60 mg, and 80 mg. (3)

4 CONTRAINDICATIONS

Known hypersensitivity to valbenazine or any components of INGREZZA or INGREZZA SPRINKLE. (4)

5 WARNINGS AND PRECAUTIONS

- Depression and suicidal ideation and behavior in patients with Huntington’s disease. (5.1)
- Hypersensitivity, including angioedema may occur. Discontinue if this occurs. (5.2)
- Somnolence/sedation: May impair patient’s ability to drive or operate hazardous machinery. (5.3)
- QT Prolongation: May cause an increase in QT interval. Avoid use in patients with congenital long QT syndrome or with arrhythmias associated with a prolonged QT interval. (5.4)
- Neuroleptic Malignant Syndrome (NMS): Discontinue if this occurs. (5.5)
- Parkinsonism: Cases of parkinson-like symptoms, some of which were severe, have been reported in the postmarketing period. Reduce the dose or discontinue INGREZZA or INGREZZA SPRINKLE treatment in patients who develop clinically significant parkinson-like signs or symptoms. (5.6)

6 ADVERSE REACTIONS

Most common adverse reaction (≥5% and twice the rate of placebo):
- Tardive dyskinesia: somnolence. (6.1)
- Chorea associated with Huntington’s disease: somnolence/lethargy/sedation, urticaria, rash, insomnia. (6.1)

To report SUSPECTED ADVERSE REACTIONS, contact Neurocrine Biosciences, Inc. at 877-641-3461 or FDA at 1-800-FDA-1088 or www.fda.gov/medwatch.

7 DRUG INTERACTIONS

Dose adjustments due to drug interactions (2.4, 7.1):

Factors | Dose Adjustments for INGREZZA and INGREZZA SPRINKLE
Use of MAOIs with INGREZZA or INGREZZA SPRINKLE | Avoid concomitant use with MAOIs.
Use of strong CYP3A4 inducers with INGREZZA or INGREZZA SPRINKLE | Concomitant use is not recommended.
Use of strong CYP3A4 inhibitors with INGREZZA or INGREZZA SPRINKLE | Recommended dosage is 40 mg once daily.
Use of strong CYP2D6 inhibitors with INGREZZA or INGREZZA SPRINKLE | Recommended dosage is 40 mg once daily.

8 USE IN SPECIFIC POPULATIONS

- Pregnancy: May cause fetal harm. (8.1)
- Lactation: Advise not to breastfeed. (8.2)

FULL PRESCRIBING INFORMATION

WARNING: DEPRESSION AND SUICIDAL IDEATION AND BEHAVIOR IN PATIENTS WITH HUNTINGTON’S DISEASE

VMAT2 inhibitors, including INGREZZA and INGREZZA SPRINKLE, can increase the risk of depression and suicidal thoughts and behavior in patients with Huntington’s disease. Anyone considering the use of INGREZZA or INGREZZA SPRINKLE must balance the risks of depression and suicidal ideation and behavior with the clinical need for treatment of chorea. Closely monitor patients for the emergence or worsening of depression, suicidal ideation, or unusual changes in behavior. Inform patients, their caregivers, and families of the risk of depression and suicidal ideation and behavior and instruct them to report behaviors of concern promptly to the treating physician.

Particular caution should be exercised in treating patients with a history of depression or prior suicide attempts or ideation, which are increased in frequency in patients with Huntington’s disease [see Warnings and Precautions (5.1)].

1 INDICATIONS AND USAGE

INGREZZA and INGREZZA SPRINKLE are indicated for the treatment of adults with:

- tardive dyskinesia [see Clinical Studies (14.1)].

- chorea associated with Huntington’s disease [see Clinical Studies (14.2)].

2 DOSAGE AND ADMINISTRATION

2.1 Recommended Dosage

Tardive Dyskinesia

The initial dosage for INGREZZA and INGREZZA SPRINKLE is 40 mg once daily. After one week, increase the dose to the recommended dosage of 80 mg once daily. A dosage of 40 mg or 60 mg once daily may be considered depending on response and tolerability.

Chorea Associated with Huntington’s Disease

The initial dosage for INGREZZA and INGREZZA SPRINKLE is 40 mg once daily. Increase the dose in 20 mg increments every two weeks to the recommended dosage of 80 mg once daily. A dosage of 40 mg or 60 mg once daily may be considered depending on response and tolerability.

2.2 Administrative Information

Administer INGREZZA and INGREZZA SPRINKLE orally with or without food [see Clinical Pharmacology (12.3)].

Administration Information for INGREZZA SPRINKLE

• Open INGREZZA SPRINKLE and sprinkle the entire contents of the capsule over a bowl containing a small amount (1 tablespoonful) of soft food such as applesauce, yogurt, or pudding. Do not sprinkle the contents of the capsule into milk or drinking water. Stir the contents of the capsule into the soft food with the tablespoon and swallow the drug/food mixture immediately. If necessary, the mixture can be stored for up to 2 hours at room temperature. Discard of any unused portion after 2 hours. Following administration of the drug/food mixture, drink a glass (e.g., 240 mL) of water.

Do not administer INGREZZA SPRINKLE via nasogastric, gastrostomy, or other enteral tubes because it may cause obstruction of enteral tubes.

• INGREZZA SPRINKLE may be swallowed whole with water. Do not crush or chew INGREZZA SPRINKLE.

2.3 Dosage Recommendations for Patients with Hepatic Impairment

The recommended dosage for patients with moderate or severe hepatic impairment (Child-Pugh score 7 to 15) is INGREZZA or INGREZZA SPRINKLE 40 mg once daily [see Use in Specific Populations (8.7), Clinical Pharmacology (12.3)].

2.4 Dosage Recommendations for Known CYP2D6 Poor Metabolizers

The recommended dosage for known CYP2D6 poor metabolizers is INGREZZA or INGREZZA SPRINKLE 40 mg once daily [see Use in Specific Populations (8.6), Clinical Pharmacology (12.3, 12.5)].

2.5 Dosage Recommendations for Concomitant Use with Strong CYP3A4 Inducers and Strong CYP3A4 or CYP2D6 Inhibitors

Coadministration with Strong CYP3A4 Inducers

Concomitant use of strong CYP3A4 inducers with INGREZZA or INGREZZA SPRINKLE is not recommended [see Drug Interactions (7.1)].

Coadministration with Strong CYP3A4 Inhibitors

The recommended dosage for patients receiving strong CYP3A4 inhibitors is INGREZZA or INGREZZA SPRINKLE 40 mg once daily [see Drug Interactions (7.1)].

Coadministration with Strong CYP2D6 Inhibitors

The recommended dosage for patients receiving strong CYP2D6 inhibitors is INGREZZA or INGREZZA SPRINKLE 40 mg once daily [see Drug Interactions (7.1)].

3 DOSAGE FORMS AND STRENGTHS

INGREZZA

- 40 mg capsule: white opaque body and purple cap, printed with ‘VBZ’ and ‘40’ in black ink. Each capsule contains 40 mg valbenazine.
- 60 mg capsule: dark red opaque body and purple cap, printed with ‘VBZ’ and ‘60’ in black ink. Each capsule contains 60 mg valbenazine.
- 80 mg capsule: purple opaque body and cap, printed with ‘VBZ’ and ‘80’ in black ink. Each capsule contains 80 mg valbenazine.

INGREZZA SPRINKLE

- 40 mg capsule: pearl white opaque cap and body, printed with a band, directional arrows, and “VBZ 40” in black ink on both the cap and body. Each capsule contains 40 mg valbenazine.
- 60 mg capsule: pearl white opaque cap and body, printed with a band, directional arrows, and “VBZ 60” in dark red ink on both the cap and body. Each capsule contains 60 mg valbenazine.
- 80 mg capsule: pearl white opaque cap and body, printed with a band, directional arrows, and “VBZ 80” in purple ink on both the cap and body. Each capsule contains 80 mg valbenazine.

4 CONTRAINDICATIONS

INGREZZA and INGREZZA SPRINKLE are contraindicated in patients with a history of hypersensitivity to valbenazine or any components of INGREZZA or INGREZZA SPRINKLE. Rash, urticaria, and reactions consistent with angioedema (e.g., swelling of the face, lips, and mouth) have been reported with use of INGREZZA [see Warnings and Precautions (5.2) and Adverse Reactions (6.2)].

5 WARNINGS AND PRECAUTIONS

5.1 Depression and Suicidal Ideation and Behavior in Patients with Huntington’s Disease

Patients with Huntington’s disease are at increased risk for depression, and suicidal ideation or behaviors. VMAT2 inhibitors, including INGREZZA and INGREZZA SPRINKLE, can increase the risk for suicidal ideation and behaviors in patients with Huntington’s disease.

In a 14-week, double-blind, placebo-controlled trial [see Clinical Studies (14.2)], depression or depressed mood was reported in 4.7% of patients taking INGREZZA compared to 1.6% of patients who received placebo, and no patients taking INGREZZA reported suicidal ideation or behavior compared to 1 patient (1.6%) who received placebo. Patients with significant risk for suicidal behavior or with unstable psychiatric symptoms were excluded from this trial. Suicidal ideation (9 subjects; 7.2%) and suicide attempts (3 subjects; 2.4%) were reported in the longer open-label extension trial (N=125).

When considering the use of INGREZZA or INGREZZA SPRINKLE, the risk of suicidal ideation and behaviors must be balanced against the need for treatment of chorea. All patients treated with INGREZZA and INGREZZA SPRINKLE should be observed for new or worsening depression, suicidal ideation or behaviors. If any of these reactions occur and do not resolve, consider discontinuing treatment with INGREZZA or INGREZZA SPRINKLE.

5.2 Hypersensitivity Reactions

Hypersensitivity reactions, including cases of angioedema involving the larynx, glottis, lips, and eyelids, have been reported in the postmarketing setting in patients after taking the first or subsequent doses of INGREZZA [see Adverse Reactions (6.2)]. A case of angioedema involving the lips and face, with rash and shortness of breath was reported in a patient with Huntington’s disease taking INGREZZA during a clinical study. Urticaria and rash were also reported during a clinical study in patients with Huntington’s disease. Angioedema associated with laryngeal edema can be fatal. If any of these reactions occur, discontinue INGREZZA or INGREZZA SPRINKLE.

5.3 Somnolence and Sedation

INGREZZA and INGREZZA SPRINKLE can cause somnolence and sedation, which was the most common adverse reaction in placebo-controlled trials with INGREZZA [see Adverse Reactions (6.1)]. Patients should not perform activities requiring mental alertness such as operating a motor vehicle or operating hazardous machinery until they know how they will be affected by INGREZZA or INGREZZA SPRINKLE.

5.4 QT Prolongation

INGREZZA and INGREZZA SPRINKLE may prolong the QT interval, although the degree of QT prolongation is not clinically significant at concentrations expected with recommended dosing. In patients taking a strong CYP2D6 or CYP3A4 inhibitor, or who are CYP2D6 poor metabolizers, INGREZZA and INGREZZA SPRINKLE concentrations may be higher and QT prolongation clinically significant [see Clinical Pharmacology (12.2)]. For patients who are CYP2D6 poor metabolizers or are taking a strong CYP2D6 inhibitor, dose reduction may be necessary. For patients taking a strong CYP3A4 inhibitor, reduce the dose of INGREZZA or INGREZZA SPRINKLE to 40 mg once daily [see Dosage and Administration (2.4, 2.5)]. INGREZZA and INGREZZA SPRINKLE should be avoided in patients with congenital long QT syndrome or with arrhythmias associated with a prolonged QT interval. For patients at increased risk of a prolonged QT interval, assess the QT interval before increasing the dosage.

5.5 Neuroleptic Malignant Syndrome (NMS)

A potentially fatal symptom complex referred to as Neuroleptic Malignant Syndrome (NMS) has been reported in association with drugs that reduce dopaminergic transmission. In the postmarketing setting, NMS has been reported in patients taking VMAT2 inhibitors, including INGREZZA. Clinicians should be alerted to the signs and symptoms associated with NMS. Clinical manifestations of NMS are hyperpyrexia, muscle rigidity, altered mental status, and evidence of autonomic instability (irregular pulse or blood pressure, tachycardia, diaphoresis, and cardiac dysrhythmia). Additional signs may include elevated creatine phosphokinase, myoglobinuria, rhabdomyolysis, and acute renal failure. The diagnosis of NMS can be complicated; other serious medical illness (e.g., pneumonia, systemic infection) and untreated or inadequately treated extrapyramidal disorders can present with similar signs and symptoms. Other important considerations in the differential diagnosis include central anticholinergic toxicity, heat stroke, drug fever, and primary central nervous system pathology.

The management of NMS should include (1) immediate discontinuation of INGREZZA or INGREZZA SPRINKLE; (2) intensive symptomatic treatment and medical monitoring; and (3) treatment of any concomitant serious medical problems for which specific treatments are available. There is no general agreement about specific pharmacological treatment regimens for NMS.

Recurrence of NMS has been reported with resumption of drug therapy. If treatment with INGREZZA or INGREZZA SPRINKLE is needed after recovery from NMS, patients should be monitored for signs of recurrence.

5.6 Parkinsonism

INGREZZA and INGREZZA SPRINKLE may cause parkinsonism. Parkinsonism has also been observed with other VMAT2 inhibitors. In the 3 placebo-controlled clinical studies in patients with tardive dyskinesia, the incidence of parkinson-like adverse events was 3% of patients treated with INGREZZA and <1% of placebo-treated patients.

In a placebo-controlled clinical study in patients with chorea associated with Huntington’s disease, the incidence of parkinson-like adverse events was 4.7% in patients treated with INGREZZA and 0% in placebo-treated patients. Because rigidity can develop as part of the underlying disease process in Huntington’s disease, it may be difficult to distinguish between potential drug-induced parkinsonism and progression of underlying Huntington’s disease. Drug-induced parkinsonism has the potential to cause more functional disability than untreated chorea for some patients with Huntington’s disease.

Postmarketing safety reports have described parkinson-like symptoms in patients taking INGREZZA for tardive dyskinesia, some of which were severe and required hospitalization. In most cases, severe parkinsonism occurred within the first two weeks after starting or increasing the dose of INGREZZA. Associated symptoms have included falls, gait disturbances, tremor, drooling and hypokinesia. In cases in which follow-up clinical information was available, parkinson-like symptoms were reported to resolve following discontinuation of INGREZZA therapy.

Reduce the dose or discontinue INGREZZA or INGREZZA SPRINKLE treatment in patients who develop clinically significant parkinson-like signs or symptoms.

6 ADVERSE REACTIONS

The following clinically significant adverse reactions are discussed in more detail in other sections of the labeling:

- Depression and Suicidal Ideation and Behavior in Patients with Huntington’s Disease [see Boxed Warning and Warnings and Precautions (5.1)]
- Hypersensitivity Reactions [see Contraindications (4) and Warnings and Precautions (5.2)]
- Somnolence and Sedation [see Warnings and Precautions (5.3)]
- QT Prolongation [see Warnings and Precautions (5.4)]
- Neuroleptic Malignant Syndrome (NMS) [see Warnings and Precautions (5.5)]
- Parkinsonism [see Warnings and Precautions (5.6)]

6.1 Clinical Trials Experience

Because clinical trials are conducted under widely varying conditions, adverse reaction rates observed in the clinical trials of a drug cannot be directly compared to rates in the clinical trials of another drug and may not reflect the rates observed in practice.

The safety of INGREZZA SPRINKLE has been established from adequate and well-controlled studies of INGREZZA [see Clinical Studies (14)]. Below is a display of the adverse reactions of INGREZZA in these adequate and well-controlled studies.

Tardive Dyskinesia

Variable and Fixed Dose Placebo-Controlled Trial Experience

The safety of INGREZZA was evaluated in 3 placebo-controlled studies, each 6 weeks in duration (fixed dose, dose escalation, dose reduction), including 445 patients. Patients were 26 to 84 years of age with moderate to severe tardive dyskinesia and had concurrent diagnoses of mood disorder (27%) or schizophrenia/ schizoaffective disorder (72%). The mean age was 56 years. Patients were 57% Caucasian, 39% African-American, and 4% other. With respect to ethnicity, 28% were Hispanic or Latino. All subjects continued previous stable regimens of antipsychotics; 85% and 27% of subjects, respectively, were taking atypical and typical antipsychotic medications at study entry.

Adverse Reactions Leading to Discontinuation of Treatment

A total of 3% of INGREZZA-treated patients and 2% of placebo-treated patients discontinued because of adverse reactions.

Common Adverse Reactions

Adverse reactions that occurred in the 3 placebo-controlled studies at an incidence of ≥2% and greater than placebo are presented in Table 1.

Table 1: Adverse Reactions in 3 Placebo-Controlled Studies of 6-week Treatment Duration Reported at ≥2% and >Placebo – Tardive Dyskinesia
Adverse Reaction^1 | INGREZZA (n=262) % | Placebo (n=183) %
General Disorders
Somnolence (somnolence, fatigue, sedation) | 10.9 | 4.2
Nervous System Disorders
Anticholinergic effects | 5.4 | 4.9
(dry mouth, constipation, disturbance in attention, vision
blurred, urinary retention)
Balance disorders/fall (fall, gait disturbance, dizziness, balance disorder) | 4.1 | 2.2
Headache | 3.4 | 2.7
Akathisia (akathisia, restlessness) | 2.7 | 0.5
Gastrointestinal Disorders
Vomiting | 2.6 | 0.6
Nausea | 2.3 | 2.1
Musculoskeletal Disorders
Arthralgia | 2.3 | 0.5

^1 Within each adverse reaction category, the observed adverse reactions are listed in order of decreasing frequency.

Other Adverse Reactions Observed During the Premarketing Evaluation of INGREZZA

Other adverse reactions of ≥1% incidence and greater than placebo are shown below. The following list does not include adverse reactions: 1) already listed in previous tables or elsewhere in the labeling, 2) for which a drug cause was remote, 3) which were so general as to be uninformative, 4) which were not considered to have clinically significant implications, or 5) which occurred at a rate equal to or less than placebo.

Endocrine Disorders: blood glucose increased

General Disorders: weight increased

Infectious Disorders: respiratory infections

Neurologic Disorders: drooling, dyskinesia, extrapyramidal symptoms (non-akathisia)

Psychiatric Disorders: anxiety, insomnia

During the tardive dyskinesia controlled trials, there was a dose-related increase in prolactin. Additionally, in these trials there was a dose-related increase in alkaline phosphatase and bilirubin, suggesting a potential risk for cholestasis.

Chorea Associated with Huntington’s Disease

The safety of INGREZZA was evaluated in a 14-week placebo-controlled study including 127 patients with chorea associated with Huntington’s disease. Patients were 25 to 75 years of age. The mean age was 54 years. Patients were 96% Caucasian, 1% African-American, 1% Asian, and 2% Other. With respect to ethnicity, 6% were Hispanic or Latino.

Adverse Reactions Leading to Discontinuation of Treatment

A total of 8% of INGREZZA-treated patients and 6% of placebo-treated patients discontinued because of adverse reactions.

Common Adverse Reactions

Adverse reactions that occurred in the placebo-controlled study at an incidence of ≥4% and greater than placebo are presented in Table 2.

Table 2: Adverse Reactions in the Placebo-Controlled Study of 12-week Treatment Duration Reported at ≥4% and >Placebo – Chorea Associated with Huntington’s Disease
Adverse Reaction | INGREZZA (n=64) % | Placebo (n=63) %
Nervous System Disorders
Somnolence, lethargy, sedation | 18.8 | 3.2
Akathisia | 6.3 | 4.8
General Disorders and Administration Site Conditions
Fatigue | 14.1 | 9.5
Skin and Subcutaneous Tissue Disorders
Urticaria | 9.4 | 0
Rash | 7.8 | 0
Gastrointestinal Disorders
Diarrhea | 4.7 | 1.6
Nausea | 4.7 | 0
Psychiatric Disorders
Insomnia, middle insomnia | 6.3 | 1.6
Depression, depressed mood | 4.7 | 1.6
Musculoskeletal Disorders
Back pain | 4.7 | 0

6.2 Postmarketing Experience

The following adverse reactions have been identified during post-approval use of INGREZZA that are not included in other sections of labeling. Because these reactions are reported voluntarily from a population of uncertain size, it is not always possible to reliably estimate their frequency or establish a causal relationship to drug exposure.

Immune System Disorders: hypersensitivity reactions (including allergic dermatitis and pruritis)

7 DRUG INTERACTIONS

7.1 Drugs Having Clinically Important Interactions with INGREZZA and INGREZZA SPRINKLE

Table 3: Clinically Significant Drug Interactions with INGREZZA and INGREZZA SPRINKLE
Monoamine Oxidase Inhibitors (MAOIs)
Clinical Implication: | Concomitant use of INGREZZA or INGREZZA SPRINKLE with MAOIs may increase the concentration of monoamine neurotransmitters in synapses, potentially leading to increased risk of adverse reactions such as serotonin syndrome, or attenuated treatment effect of INGREZZA or INGREZZA SPRINKLE.
Prevention or Management: | Avoid concomitant use of INGREZZA or INGREZZA SPRINKLE with MAOIs, or within 14 days of discontinuing therapy with an MAOI.
Strong CYP3A4 Inhibitors
Clinical Implication: | Concomitant use of INGREZZA or INGREZZA SPRINKLE with strong CYP3A4 inhibitors increased the exposure (Cmax and AUC) to valbenazine and its active metabolite compared with the use of INGREZZA or INGREZZA SPRINKLE alone [see Clinical Pharmacology (12.3)]. Increased exposure of valbenazine and its active metabolite may increase the risk of exposure-related adverse reactions [see Warnings and Precautions (5.4)].
Prevention or Management: | Reduce INGREZZA or INGREZZA SPRINKLE dose when INGREZZA or INGREZZA SPRINKLE is coadministered with a strong CYP3A4 inhibitor [see Dosage and Administration (2.5)].
Strong CYP2D6 Inhibitors
Clinical Implication: | Concomitant use of INGREZZA or INGREZZA SPRINKLE with strong CYP2D6 inhibitors increased the exposure (Cmax and AUC) to valbenazine’s active metabolite compared with the use of INGREZZA or INGREZZA SPRINKLE alone [see Clinical Pharmacology (12.3, 12.5)]. Increased exposure of active metabolite may increase the risk of exposure-related adverse reactions [see Warnings and Precautions (5.4)].
Prevention or Management: | Reduce INGREZZA or INGREZZA SPRINKLE dose when INGREZZA or INGREZZA SPRINKLE is coadministered with a strong CYP2D6 inhibitor [see Dosage and Administration (2.5)].
Strong CYP3A4 Inducers
Clinical Implication: | Concomitant use of INGREZZA or INGREZZA SPRINKLE with a strong CYP3A4 inducer decreased the exposure of valbenazine and its active metabolite compared to the use of INGREZZA or INGREZZA SPRINKLE alone. Reduced exposure of valbenazine and its active metabolite may reduce efficacy [see Clinical Pharmacology (12.3)].
Prevention or Management: | Concomitant use of strong CYP3A4 inducers with INGREZZA or INGREZZA SPRINKLE is not recommended [see Dosage and Administration (2.5)].
Digoxin
Clinical Implication: | Concomitant use of INGREZZA or INGREZZA SPRINKLE with digoxin increased digoxin levels because of inhibition of intestinal P-glycoprotein (P-gp) [see Clinical Pharmacology (12.3)].
Prevention or Management: | Digoxin concentrations should be monitored when co-administering INGREZZA or INGREZZA SPRINKLE with digoxin. Increased digoxin exposure may increase the risk of exposure-related adverse reactions. Dosage adjustment of digoxin may be necessary.

8 USE IN SPECIFIC POPULATIONS

8.1 Pregnancy

Risk Summary

The limited available data on INGREZZA or INGREZZA SPRINKLE use in pregnant women are insufficient to inform a drug-associated risk. In animal reproductive studies, no malformations were observed when valbenazine was administered orally to rats and rabbits during the period of organogenesis at doses up to 1.8 or 24 times, respectively, the maximum recommended human dose (MRHD) of 80 mg/day based on mg/m^2 body surface area. However, administration of valbenazine to pregnant rats during organogenesis through lactation produced an increase in the number of stillborn pups and postnatal pup mortalities at doses <1 times the MRHD based on mg/m^2 [see Data]. Advise a pregnant woman of the potential risk to a fetus.

The estimated background risk of major birth defects and miscarriage for the indicated population is unknown. All pregnancies have a background risk of birth defect, loss, or other adverse outcomes. The background risk of major birth defects and miscarriage in the U.S. general population is 2 to 4% and 15 to 20% of clinically recognized pregnancies, respectively.

Data

Animal Data

Valbenazine was administered orally to pregnant rats during the period of organogenesis at 1, 5, and 15 mg/kg/day, which are approximately 0.1, 0.6, and 2 times the MRHD of 80 mg/day based on mg/m^2 body surface area. Valbenazine produced a significant decrease in maternal body weight gain at 0.6 and 2 times the MRHD of 80 mg/day based on mg/m^2. No adverse embryo fetal effects were produced when valbenazine was administered at doses up to 2 times the MRHD of 80 mg/day based on mg/m^2.

Valbenazine was administered orally to pregnant rabbits during the period of organogenesis at 20, 50, and 100 mg/kg/day, which are approximately 5, 12, and 24 times the MRHD of 80 mg/day based on mg/m^2. No malformations were observed at doses up to 24 times the MRHD of 80 mg/day based on mg/m^2. However, valbenazine produced a delay in fetal development (decreased fetal weights and delayed ossification) at 24 times the MRHD of 80 mg/day based on mg/m^2, likely secondary to maternal toxicity (decreased food intake and loss in body weight).

Valbenazine was administered orally to pregnant rats during the period of organogenesis through lactation (day 7 of gestation through day 20 postpartum) at 1, 3, and 10 mg/kg/day, which are approximately 0.1, 0.4, and 1.2 times the MRHD of 80 mg/day based on mg/m^2. Valbenazine produced an increase in the incidence of stillbirths and postnatal pup mortality at 0.4 and 1.2 times the MRHD of 80 mg/day based on mg/m^2. Valbenazine did not affect neurobehavioral function including learning and memory and had no effect on sexual maturation at doses <1 times the MRHD of 80 mg/day based on mg/m^2 (because of death in the majority of the high dose group (1.2 times the MRHD), these parameters were not assessed in this group).

8.2 Lactation

Risk Summary

There is no information regarding the presence of valbenazine or its metabolites in human milk, the effects on the breastfed infant, or the effects on milk production. Valbenazine and its metabolites have been detected in rat milk at concentrations higher than in plasma following oral administration of valbenazine at doses 0.1 to 1.2 times the MRHD based on mg/m^2. Based on animal findings of increased perinatal mortality in exposed fetuses and pups, advise a woman not to breastfeed during treatment with INGREZZA or INGREZZA SPRINKLE and for 5 days after the final dose.

8.4 Pediatric Use

Safety and effectiveness of INGREZZA and INGREZZA SPRINKLE have not been established in pediatric patients.

8.5 Geriatric Use

No dose adjustment of INGREZZA or INGREZZA SPRINKLE is required for elderly patients.

Tardive Dyskinesia

In 3 randomized, placebo-controlled studies of INGREZZA in patients with tardive dyskinesia, 16% of patients were 65 years and older. The safety and effectiveness were similar in patients older than 65 years compared to younger patients.

Huntington’s Disease

In the randomized, placebo-controlled study of INGREZZA in 127 patients with chorea associated with Huntington’s disease, 15% were 65 years and older. This study did not include sufficient numbers of subjects aged 65 and older to determine whether they responded differently from younger subjects [see Clinical Studies (14.2)].

8.6 CYP2D6 Poor Metabolizers

Dosage reduction of INGREZZA and INGREZZA SPRINKLE is recommended for known CYP2D6 poor metabolizers [see Dosage and Administration (2.4)]. Increased exposure (Cmax and AUC) to valbenazine’s active metabolite was observed in CYP2D6 poor metabolizers. Increased exposure of active metabolite may increase the risk of exposure-related adverse reactions [see Clinical Pharmacology (12.3, 12.5)].

8.7 Hepatic Impairment

Dosage reduction of INGREZZA and INGREZZA SPRINKLE is recommended for patients with moderate or severe hepatic impairment [see Dosage and Administration (2.3)]. Patients with moderate to severe hepatic impairment (Child-Pugh score 7 to 15) had higher exposure of valbenazine and its active metabolite than patients with normal hepatic function [see Clinical Pharmacology (12.3)].

8.8 Renal Impairment

Dosage adjustment is not necessary for patients with mild, moderate, or severe renal impairment. INGREZZA and INGREZZA SPRINKLE do not undergo primary renal clearance. [see Clinical Pharmacology (12.3)].

10 OVERDOSAGE

Human Experience

The pre-marketing clinical trials involving INGREZZA in approximately 850 subjects do not provide information regarding symptoms with overdose.

Management of Overdosage

No specific antidotes for INGREZZA or INGREZZA SPRINKLE are known. In managing overdose, provide supportive care, including close medical supervision and monitoring, and consider the possibility of multiple drug involvement. Consider contacting the Poison Help line (1-800-222-1222) or a medical toxicologist for additional overdose management recommendations.

11 DESCRIPTION

INGREZZA and INGREZZA SPRINKLE contains valbenazine, a vesicular monoamine transporter 2 (VMAT2) inhibitor, present as valbenazine tosylate salt, with the chemical name, L-Valine, (2R,3R,11bR)-1,3,4,6,7,11b-hexahydro-9,10-dimethoxy-3-(2-methylpropyl)-2H-benzo[a]quinolizin-2-yl ester, 4-methylbenzenesulfonate (1:2). Valbenazine tosylate is slightly soluble in water. Its molecular formula is C38H54N2O10S2, and its molecular weight is
762.97 g/mol (ditosylate salt) with the following structure:

The molecular formula of valbenazine free base is C24H38N2O4 and its molecular weight is 418.57.

INGREZZA is intended for oral administration only. Each capsule contains 73 mg, 109 mg or 146 mg of valbenazine tosylate equivalent to 40 mg, 60 mg or 80 mg of valbenazine free base, respectively. The capsules contain the following inactive ingredients: hypromellose, isomalt, magnesium stearate, pregelatinized starch, and silicified microcrystalline cellulose. The capsule shells contain candurin silver fine, FD&C Blue#1, FD&C Red#40, and gelatin.

INGREZZA SPRINKLE is intended for oral administration. Each capsule contains granules consisting of 73 mg, 109 mg or 146 mg of valbenazine tosylate equivalent to 40 mg, 60 mg or 80 mg of valbenazine free base, respectively. The oral granules contain the following inactive ingredients: silicified microcrystalline cellulose, isomalt, pregelatinized maize starch, hypromellose, magnesium stearate, polyvinyl alcohol, titanium dioxide, polyethylene glycol, and talc in hard gelatin capsules (contains gelatin and candurin silver fine).

12 CLINICAL PHARMACOLOGY

12.1 Mechanism of Action

The mechanism of action of valbenazine for the treatment of tardive dyskinesia and chorea in patients with Huntington’s disease is unclear, but is thought to be mediated through the reversible inhibition of vesicular monoamine transporter 2 (VMAT2), a transporter that regulates monoamine uptake from the cytoplasm to the synaptic vesicle for storage and release.

12.2 Pharmacodynamics

Valbenazine inhibits human VMAT2 (Ki ~ 150 nM) with no appreciable binding affinity for VMAT1 (Ki > 10 µM). Valbenazine is converted to the active metabolite [+]-α-dihydrotetrabenazine ([+]-α-HTBZ).
[+]-α-HTBZ also binds with relatively high affinity to human VMAT2 (Ki ~ 3 nM). Valbenazine and [+]-α-HTBZ have no appreciable binding affinity (Ki > 5000 nM) for dopaminergic (including D2), serotonergic (including 5HT2B), adrenergic, histaminergic or muscarinic receptors.

Cardiac Electrophysiology

INGREZZA and INGREZZA SPRINKLE may cause an increase in the corrected QT interval in patients who are CYP2D6 poor metabolizers or who are taking a strong CYP2D6 or CYP3A4 inhibitor. An exposure-response analysis of clinical data from two healthy volunteer studies revealed increased QTc interval with higher plasma concentrations of the active metabolite. Based on this model, patients taking an INGREZZA 60 mg or 80 mg dose with increased exposure to the metabolite (e.g., being a CYP2D6 poor metabolizer) may have a mean (upper bound of double-sided 90% CI) QT prolongation of 9.6 (12.0) msec or 11.7 (14.7) msec, respectively as compared to otherwise healthy volunteers given INGREZZA, who had a respective mean (upper bound of double-sided 90% CI) QT prolongation of 5.3 (6.7) msec or 6.7 (8.4) msec [see Warnings and Precautions (5.4)].

12.3 Pharmacokinetics

Valbenazine and its active metabolite ([+]-α-HTBZ) demonstrate approximate proportional increases for the area under the plasma concentration versus time curve (AUC) and maximum plasma concentration (Cmax) after single oral doses from 40 mg to 300 mg (i.e., 50% to 375% of the recommended treatment dose).

Absorption

INGREZZA

Following oral administration of INGREZZA, the time to reach maximum valbenazine plasma concentration (tmax) ranges from 0.5 to 1.0 hours. Valbenazine reaches steady state plasma concentrations within 1 week. The absolute oral bioavailability of valbenazine is approximately 49%. [+]-α-HTBZ gradually forms and reaches Cmax 4 to 8 hours after administration of INGREZZA.

INGREZZA SPRINKLE

Following administration of 80 mg INGREZZA SPRINKLE orally as sprinkle on applesauce, the geometric mean peak plasma concentration (Cmax) of valbenazine was 512 ng/mL, area under the plasma concentration-time curve (AUCinf) was 5,600 ng*hr/mL and the median time to reach Cmax (Tmax) was 1.5 hours. For the [+]-α-HTBZ metabolite, the geometric mean Cmax was 23 ng/mL, AUCinf was 739 ng*hr/mL and the median Tmax was 6 hours.

Following oral administration of 80 mg INGREZZA, the geometric mean Cmax, AUCinf and median Tmax of valbenazine were 744 ng/mL, 6,419 ng*hr/mL and 0.5 hour, respectively. For the [+]-α-HTBZ metabolite, the geometric mean Cmax was 26 ng/mL, AUCinf was 859 ng*hr/mL and the median Tmax was 6 hours.

When 80 mg INGREZZA SPRINKLE capsules were swallowed whole with water, the geometric mean valbenazine Cmax, AUCinf and median Tmax were 685 ng/mL, 5,981 ng*hr/mL and 1 hour, respectively. For the [+]-α-HTBZ metabolite, the geometric mean Cmax was 23 ng/mL, AUCinf was 772 ng*hr/mL and the median Tmax was 6 hours.

Effect of Food

INGREZZA

Ingestion of a high-fat meal decreases valbenazine Cmax by approximately 47% and AUC by approximately 13%. [+]-α-HTBZ Cmax and AUC are unaffected.

INGREZZA SPRINKLE

Ingestion of a high-fat meal decreases valbenazine Cmax by approximately 15% and did not have an appreciable effect on AUC. [+]-α-HTBZ Cmax and AUC are unaffected.

Distribution

The plasma protein binding of valbenazine and [+]-α-HTBZ are greater than 99% and approximately 64%, respectively. The mean steady state volume of distribution of valbenazine is 92 L.

Nonclinical data in Long-Evans rats show that valbenazine can bind to melanin-containing structures of the eye such as the uveal tract. The relevance of this observation to clinical use of INGREZZA or INGREZZA SPRINKLE is unknown.

Elimination

Valbenazine has a mean total plasma systemic clearance value of 7.2 L/hr. Valbenazine and [+]-α-HTBZ have half-lives of 15 to 22 hours.

Metabolism

Valbenazine is extensively metabolized after oral administration by hydrolysis of the valine ester to form the active metabolite ([+]-α-HTBZ) and by oxidative metabolism, primarily by CYP3A4/5, to form mono-oxidized valbenazine and other minor metabolites. [+]-α-HTBZ appears to be further metabolized in part by CYP2D6.

Excretion

Following the administration of a single 50-mg oral dose of radiolabeled C-valbenazine (i.e., ~63% of the recommended treatment dose), approximately 60% and 30% of the administered radioactivity was recovered in the urine and feces, respectively. Less than 2% was excreted as unchanged valbenazine or [+]-α-HTBZ in either urine or feces.

Specific Populations

Exposures of valbenazine in patients with hepatic and severe renal impairment are summarized in Figure 1.

Figure 1: Effects of Hepatic and Severe Renal Impairment on Valbenazine Pharmacokinetics

AUCinf=area under the plasma concentration versus time curve from 0 hours extrapolated to infinity

[+]-α-HTBZ=[+]-α-dihydrotetrabenazine (active metabolite)

Drug Interaction Studies

In Vivo Drug Interactions

The effects of paroxetine, ketoconazole and rifampin on the exposure of valbenazine are summarized in Figure 2.

Figure 2: Effects of Strong CYP2D6 and CYP3A4 Inhibitors and CYP3A4 Inducers on Valbenazine Pharmacokinetics

AUCinf=area under the plasma concentration versus time curve from 0 hours extrapolated to infinity

[+]-α-HTBZ=[+]-α-dihydrotetrabenazine (active metabolite)

The effects of valbenazine on the exposure of other coadministered drugs are summarized in Figure 3.

Figure 3: Effects of Valbenazine on Pharmacokinetics of Other Drugs

AUCinf=area under the plasma concentration versus time curve from 0 hours extrapolated to infinity

In Vitro Drug Interactions

The results of in vitro studies suggest that valbenazine and [+]-α-HTBZ are unlikely to inhibit CYP1A2, CYP2B6, CYP2C8, CYP2C9, CYP2C19, CYP2E1 or CYP3A4/5, or induce CYP1A2, CYP2B6 or CYP3A4/5 at clinically relevant concentrations.

The results of in vitro studies suggest that valbenazine and [+]-α-HTBZ are unlikely to inhibit the transporters (BCRP, OAT1, OAT3, OCT2, OATP1B1, or OATP1B3) at clinically relevant concentrations.

12.5 Pharmacogenomics

CYP2D6 metabolizes the active metabolite of valbenazine ([+]-α-HTBZ). The gene encoding CYP2D6 has polymorphisms that impact protein function. CYP2D6 poor metabolizers are individuals with two non-functioning alleles, resulting in no enzyme activity.

Pharmacokinetic data from CYP2D6 poor metabolizers (n=25) treated with valbenazine demonstrate an approximate 2-fold higher AUCinf and a 1.8-fold higher Cmax of [+]-α-HTBZ compared to normal metabolizers. Dosage reduction is recommended in CYP2D6 poor metabolizers [see Dosage and Administration (2.4), Warnings and Precautions (5.4), and Use in Specific Populations (8.6)].

In a clinical study, AUC of [+]-α-HTBZ was 22% higher and Cmax was 9% lower in intermediate metabolizers (n=7) as compared to normal metabolizers (n=11), which is not considered clinically relevant. The effects of ultrarapid metabolizer status on the pharmacokinetics of [+]-α-HTBZ have not been studied.

Approximately 7% of White populations, 2% of Asian populations, and 2% of African-American populations are poor metabolizers.

13 NONCLINICAL TOXICOLOGY

13.1 Carcinogenesis, Mutagenesis, Impairment of Fertility

Carcinogenesis

Valbenazine did not increase tumors in rats treated orally for 91 weeks at 0.5, 1, and 2 mg/kg/day. These doses are <1 times (0.06, 0.1, and 0.24 times, respectively) the MRHD of 80 mg/day based on mg/m^2.

Valbenazine did not increase tumors in hemizygous Tg.rasH2 mice treated orally for 26 weeks at 10, 30 and 75 mg/kg/day, which are 0.6, 1.9 and 4.6 times the MRHD of 80 mg/day based on mg/m^2.

Mutagenesis

Valbenazine was not mutagenic in the in vitro bacterial reverse mutation test (Ames) or clastogenic in the in vitro mammalian chromosomal aberrations assay in human peripheral blood lymphocytes or in the in vivo rat bone marrow micronucleus assay.

Impairment of Fertility

In a fertility study, rats were treated orally with valbenazine at 1, 3, and 10 mg/kg/day prior to mating and through mating, for a minimum of 10 weeks (males) or through Day 7 of gestation (females). These doses are 0.1, 0.4, and 1.2 times the MRHD of 80 mg/day based on mg/m^2, respectively. Valbenazine delayed mating in both sexes, which led to lower number of pregnancies and disrupted estrous cyclicity at the high dose, 1.2 times the MRHD of 80 mg/day based on mg/m^2. Valbenazine had no effects on sperm parameters (motility, count, density) or on uterine parameters (corpora lutea, number of implants, viable implants, pre-implantation loss, early resorptions and post-implantation loss) at any dose.

14 CLINICAL STUDIES

14.1 Tardive Dyskinesia

INGREZZA SPRINKLE

The effectiveness of INGREZZA SPRINKLE has been established from adequate and well-controlled studies of INGREZZA for the treatment of tardive dyskinesia. Presented below is a display of the efficacy results of the adequate and well-controlled studies of INGREZZA in patients with tardive dyskinesia.

INGREZZA

A randomized, double-blind, placebo-controlled trial of INGREZZA was conducted in patients with moderate to severe tardive dyskinesia as determined by clinical observation. Patients had underlying schizophrenia, schizoaffective disorder, or a mood disorder. Individuals at significant risk for suicidal or violent behavior and individuals with unstable psychiatric symptoms were excluded.

The Abnormal Involuntary Movement Scale (AIMS) was the primary efficacy measure for the assessment of tardive dyskinesia severity. The AIMS is a 12-item scale; items 1 to 7 assess the severity of involuntary movements across body regions and these items were used in this study. Each of the 7 items was scored on a 0 to 4 scale, rated as: 0=no dyskinesia; 1=low amplitude, present during some but not most of the exam; 2=low amplitude and present during most of the exam (or moderate amplitude and present during some of the exam); 3=moderate amplitude and present during most of exam; or 4=maximal amplitude and present during most of exam. The AIMS dyskinesia total score (sum of items 1 to 7) could thus range from 0 to 28, with a decrease in score indicating improvement. The AIMS was scored by central raters who interpreted the videos blinded to subject identification, treatment assignment, and visit number.

The primary efficacy endpoint was the mean change from baseline in the AIMS dyskinesia total score at the end of Week 6. The change from baseline for two fixed doses of INGREZZA (40 mg or 80 mg) was compared to placebo. At the end of Week 6, subjects initially assigned to placebo were re-randomized to receive INGREZZA 40 mg or 80 mg. Subjects originally randomized to INGREZZA continued INGREZZA at their randomized dose. Follow-up was continued through Week 48 on the assigned drug, followed by a 4-week period off-drug (subjects were not blind to withdrawal).

A total of 234 subjects were enrolled, with 29 (12%) discontinuing prior to completion of the placebo-controlled period. Mean age was 56 (range 26 to 84). Patients were 54% male and 46% female. Patients were 57% Caucasian, 38% African-American, and 5% other. Concurrent diagnoses included schizophrenia/schizoaffective disorder (66%) and mood disorder (34%). With respect to concurrent antipsychotic use, 70% of subjects were receiving atypical antipsychotics, 14% were receiving typical or combination antipsychotics, and 16% were not receiving antipsychotics.

Results are presented in Table 4, with the distribution of responses shown in Figure 4. The change from baseline in the AIMS total dyskinesia score in the 80 mg INGREZZA group was statistically significantly different from the change in the placebo group. Subgroup analyses by gender, age, racial subgroup, underlying psychiatric diagnostic category, and concomitant antipsychotic medication did not suggest any clear evidence of differential responsiveness.

The mean changes in the AIMS dyskinesia total score by visit are shown in Figure 5. Among subjects remaining in the study at the end of the 48-week treatment (N=123 [52.6%]), following discontinuation of INGREZZA, the mean AIMS dyskinesia total score appeared to return toward baseline (there was no formal hypothesis testing for the change following discontinuation).

Table 4: Primary Efficacy Endpoint – Severity of Tardive Dyskinesia at Baseline and the End of Week 6
Endpoint | Treatment Group | Mean Baseline Score (SD) | LS Mean Change from Baseline (SEM)** | Placebo-subtracted Difference (95% CI)
AIMS Dyskinesia Total Score | INGREZZA 40 mg | 9.8 (4.1) | -1.9 (0.4) | -1.8 (-3.0, -0.7)
 | INGREZZA 80 mg* | 10.4 (3.6) | -3.2 (0.4) | -3.1 (-4.2, -2.0)
 | Placebo | 9.9 (4.3) | -0.1 (0.4)

LS Mean=least-squares mean; SD=standard deviation; SEM=standard error of the mean; CI=2-sided 95% confidence interval
*Dose that was statistically significantly different from placebo after adjusting for multiplicity.
**A negative change from baseline indicates improvement.

Figure 4: Percent of Patients with Specified Magnitude of AIMS Total Score Improvement at the End of Week 6

ITT=Intent to Treat; This analysis set includes all randomized patients who had a baseline and at least one post-baseline AIMS dyskinesia total score value reported.

Figure 5: AIMS Dyskinesia Total Score Mean Change from Baseline – Entire Study Duration (Arithmetic Mean)

DB=Double-Blind; After Week 6, subjects initially receiving placebo were re-randomized to receive INGREZZA 40 mg or 80 mg until the end of Week 48. Error bars represent ±1 Standard Error of the Mean (SEM).

Efficacy of INGREZZA 60 mg

Based on modeling and simulation, the predicted mean change from baseline in the AIMS dyskinesia total score at Week 6 for INGREZZA 60 mg once daily in subjects with TD is -2.69 (95% CI: -3.30, -2.13), which is within the efficacy range for INGREZZA 40 mg and 80 mg once daily.

14.2 Chorea Associated with Huntington’s Disease

INGREZZA SPRINKLE

The effectiveness of INGREZZA SPRINKLE has been established from adequate and well-controlled studies of INGREZZA for the treatment of chorea associated with Huntington’s disease. Presented below is a display of the efficacy results of the adequate and well-controlled studies of INGREZZA in patients with chorea associated with Huntington’s disease.

INGREZZA

A randomized, double-blind, placebo-controlled study was conducted to evaluate the efficacy, safety, and tolerability of INGREZZA in patients with chorea associated with Huntington’s disease (NCT04102579). Treatment duration was 12 weeks followed by a 2-week period off drug. INGREZZA was started at 40 mg per day and the dose could be increased every 2 weeks in 20 mg increments up to a maximum dosage of 80 mg per day. The primary efficacy endpoint was the change from baseline to the end of the treatment period (average of Week 10 and Week 12) in the Total Maximal Chorea score of the Unified Huntington’s Disease Rating Scale (UHDRS). The Total Maximal Chorea score is rated from 0 to 4 (with 0 representing no chorea) for 7 different parts of the body, with a total score ranging from 0 to 28.

A total of 128 patients were randomized into the study, and 125 patients were included in the analysis of efficacy. In these patients, the mean age was 54 years (range 25 to 74 years), 46% were male and 96% were White. Greater than 80% of patients were taking the 80 mg daily dosage at the end of the 12-week treatment period.

Table 5 and Figure 6 summarize the effects of INGREZZA on chorea based on the Total Maximal Chorea score.

The mean change in Total Maximal Chorea scores for patients receiving INGREZZA improved by 4.6 units (LS mean) from baseline to the end of the treatment period (average of Week 10 and Week 12), compared to 1.4 units in the placebo group. The treatment effect of -3.2 units was statistically significant (p<0.0001) (Figure 6). At the Week 14 follow-up visit (2 weeks after discontinuation of the study medication), the Total Maximal Chorea scores of patients who had received INGREZZA returned to baseline.

Table 5: Primary Efficacy Endpoint - Mean Change from Baseline to End of Treatment in Total Maximal Chorea Score in Patients with Huntington’s Disease Treated with INGREZZA
Primary Endpoint | Treatment Group | Mean Baseline Score (SD) | LS Mean Change from Baseline (SEM) b | Placebo-subtracted Difference (95% CI)
TMC Scorea | INGREZZA N=64 | 12.2 (2.3) | -4.6 (0.4) | -3.2 (-4.4, -2.0) p <0.0001
 | Placebo N=61 | 12.1 (2.8) | -1.4 (0.4)

a TMC, Total Maximal Chorea is a subscale of the Unified Huntington’s Disease Rating Scale (UHDRS)
b LS Mean=least-squares mean; SD=standard deviation; SEM=standard error of the mean; CI=2-sided 95% confidence interval

Figure 6: Mean Change in Total Maximal Chorea Score Over Time

LSMD=least-squares mean difference (SEM) [INGREZZA – Placebo]

CI=confidence interval

SEM=standard error of the mean

Figure 7: Distribution of the Change in Total Maximal Chorea Score (Average of Week 10 and 12)

Figure 7 shows the distribution of values for the change in Total Maximal Chorea Score. Negative values indicate a reduction in chorea and positive values indicate an increase in chorea.

In a clinician-rated global impression of change (CGI-C), clinicians rated 43% of patients treated with INGREZZA as “Much Improved” or “Very Much Improved” at the end of treatment, compared to 13% of patients who received placebo (p<0.001).

A patient-rated global impression of change (PGI-C) assessed how patients rated their overall chorea symptoms. Of the patients treated with INGREZZA, 53% rated their symptoms as “Much Improved” or “Very Much Improved” at the end of treatment, compared to 26% of patients who received placebo (p <0.01).

16 HOW SUPPLIED/STORAGE AND HANDLING

How Supplied

INGREZZA (valbenazine) capsules are available as:

40 mg Capsule: White opaque body with a purple cap, printed with ‘VBZ’ and ‘40’ in black ink.

60 mg Capsule: Dark red opaque body with a purple cap, printed with ‘VBZ’ and ‘60’ in black ink.

80 mg Capsule: Purple opaque body and cap, printed with ‘VBZ’ and ‘80’ in black ink.

INGREZZA SPRINKLE (valbenazine) capsules are available as:

40 mg Capsule: Pearl white opaque cap and body, printed with a band, directional arrows, and “VBZ 40” in black ink on both the cap and body.

60 mg Capsule: Pearl white opaque cap and body, printed with a band, directional arrows, and “VBZ 60” in dark red ink on both the cap and body.

80 mg Capsule: Pearl white opaque cap and body, printed with a band, directional arrows, and “VBZ 80” in purple ink on both the cap and body.

Table 6: INGREZZA and INGREZZA SPRINKLE Configurations and NDC Numbers

Package Configuration | Capsule Strength | NDC Number
INGREZZA
Bottle of 30 | 40 mg | NDC 70370-2040-1
Bottle of 30 | 60 mg | NDC 70370-1060-1
Bottle of 30 | 80 mg | NDC 70370-1080-1
4-week Initiation Pack for tardive dyskinesia | 28-day blister pack containing: 7 x 40 mg and 21 x 80 mg | NDC 70370-2048-6
4-week Initiation Pack for chorea associated with Huntington’s disease | 28-day blister pack containing: 14 x 40 mg and 14 x 60 mg | NDC 70370-2046-1
INGREZZA SPRINKLE
Bottle of 30 | 40 mg | NDC 70370-4040-1
Bottle of 30 | 60 mg | NDC 70370-4060-1
Bottle of 30 | 80 mg | NDC 70370-4080-1

Storage

INGREZZA: Store at 15°C to 30°C (59°F to 86°F).

INGREZZA SPRINKLE: Store at 20°C to 25°C (68°F to 77°F). Excursions permitted between 15°C and 30°C (59°F and 86°F). Protect from moisture. Dispense in original container or in a tight container as defined in USP.

17 PATIENT COUNSELING INFORMATION

Advise the patient to read the FDA-approved patient labeling (Medication Guide and Instructions for Use).

Depression and Suicidal Ideation and Behavior in Patients with Huntington’s Disease

Inform patients, their caregivers, and families of the risks of depression, worsening depression, and suicidal ideation and behavior associated with INGREZZA and INGREZZA SPRINKLE, and instruct them to report behaviors of concern promptly to the treating physician. Patients with Huntington’s disease who express suicidal ideation should be evaluated immediately [see Warnings and Precautions (5.1)].

Hypersensitivity Reactions

Inform patients about the signs and symptoms of hypersensitivity reactions, such as angioedema, including difficulty breathing, swelling of the face, lips, eyelids, tongue or throat. Advise patients to discontinue INGREZZA or INGREZZA SPRINKLE immediately if any of these reactions occur and report to the emergency room if symptoms of angioedema occur [see Warnings and Precautions (5.2)].

Somnolence and Sedation

Inform patients that INGREZZA and INGREZZA SPRINKLE may cause somnolence and may impair the ability to perform tasks that require complex motor and mental skills. Advise patients that until they learn how they respond to INGREZZA or INGREZZA SPRINKLE, they should be careful or avoid doing activities that require them to be alert, such as driving a car or operating machinery [see Warnings and Precautions (5.3)].

Prolongation of the QT Interval

Inform patients to consult their physician immediately if they feel faint, lose consciousness, or have heart palpitations [see Warnings and Precautions (5.4)]. Advise patients to inform physicians that they are taking INGREZZA or INGREZZA SPRINKLE before any new drug is taken.

Neuroleptic Malignant Syndrome (NMS)

Counsel patients about a potentially fatal adverse reaction – neuroleptic malignant syndrome (NMS) – that has been reported in association with administration of VMAT2 inhibitors, including INGREZZA and INGREZZA SPRINKLE. Advise patients to contact a healthcare provider or report to the emergency room if they experience signs or symptoms of NMS [see Warnings and Precautions (5.5)].

Parkinsonism

Inform patients that parkinson-like symptoms may occur while taking INGREZZA or INGREZZA SPRINKLE. Advise patients to consult their healthcare provider if they experience difficulty moving or loss of ability to move muscles voluntarily, tremor, gait disturbances, or drooling [see Warnings and Precautions (5.6)].

Pregnancy

Advise a pregnant patient of the potential risk to a fetus [see Use in Specific Populations (8.1)].

Lactation

Advise a woman not to breastfeed during treatment with INGREZZA or INGREZZA SPRINKLE and for 5 days after the final dose [see Use in Specific Populations (8.2)].

Administration Information for INGREZZA SPRINKLE

Advise patients to read and follow the Instructions for Use for INGREZZA SPRINKLE.

Advise the patient of the following:

- INGREZZA SPRINKLE may be opened and the entire contents of the capsule sprinkled over a bowl containing a small amount (1 tablespoonful) of soft food such as applesauce, yogurt, or pudding. Stir the contents of the capsule into the soft food.
  ○ Do not sprinkle the contents of the capsule into milk or drinking water.
  ○ Swallow the drug/food mixture immediately.
  ○ The mixture may be stored for up to 2 hours at room temperature. Discard any unused portion after 2 hours.
  ○ Drink a glass (e.g., 240 mL) of water following administration of the drug/food mixture [see Dosage and Administration (2.2)].
- INGREZZA SPRINKLE may also be swallowed whole with water [see Dosage and Administration (2.2)]. Do not crush or chew INGREZZA SPRINKLE.

For further information on INGREZZA or INGREZZA SPRINKLE, call 84-INGREZZA (844-647-3992).

Distributed by:

Neurocrine Biosciences, Inc.
6027 Edgewood Bend Court
San Diego, CA 92130

INGREZZA is a registered trademark of Neurocrine Biosciences, Inc.

098854013

MEDICATION GUIDE

INGREZZA® (in greh' zah)
(valbenazine)
capsules

INGREZZA® SPRINKLE (in greh' zah spring kuhl)
(valbenazine)
capsules

What is the most important information I should know about INGREZZA or INGREZZA SPRINKLE?

- INGREZZA or INGREZZA SPRINKLE can cause serious side effects in people with Huntington’s disease, including:
  ◦ depression
  ◦ suicidal thoughts
  ◦ suicidal actions
- Tell your healthcare provider before you start taking INGREZZA or INGREZZA SPRINKLE if you have Huntington’s disease and are depressed (have untreated depression or depression that is not well controlled by medicine) or have suicidal thoughts.
- Pay close attention to any changes, especially sudden changes, in mood, behaviors, thoughts, or feelings. This is especially important when INGREZZA or INGREZZA SPRINKLE is started and when the dose is changed.

Call your healthcare provider right away if you become depressed or have any of the following symptoms, especially if they are new, worse, or worry you:

- feel sad or have crying spells
- lose interest in seeing your friends or doing things you used to enjoy
- sleep a lot more or a lot less than usual
- feel unimportant
- feel guilty
- feel hopeless or helpless
- feel more irritable, angry or aggressive than usual
- feel more or less hungry than usual or notice a big change in your body weight
- have trouble paying attention
- feel tired or sleepy all the time
- have thoughts about hurting yourself or ending your life

What is INGREZZA or INGREZZA SPRINKLE?
INGREZZA or INGREZZA SPRINKLE is a prescription medicine used to treat adults with:

- movements in the face, tongue, or other body parts that cannot be controlled (tardive dyskinesia).
- the involuntary movements (chorea) of Huntington’s disease. INGREZZA or INGREZZA SPRINKLE does not cure the cause of the involuntary movements, and it does not treat other symptoms of Huntington’s disease, such as problems with thinking or emotions.

It is not known if INGREZZA or INGREZZA SPRINKLE is safe and effective in children.

Who should not take INGREZZA or INGREZZA SPRINKLE?
Do not take INGREZZA or INGREZZA SPRINKLE if you are allergic to valbenazine, or any of the ingredients in INGREZZA or INGREZZA SPRINKLE. See the end of this Medication Guide for a complete list of ingredients in INGREZZA or INGREZZA SPRINKLE.

Before taking INGREZZA or INGREZZA SPRINKLE, tell your healthcare provider about all of your medical conditions, including if you:

- have emotional or mental problems (for example, depression, nervousness, anxiety, anger, agitation, psychosis, previous suicidal thoughts or suicide attempts)
- have liver problems
- have heart disease that is not stable, have heart failure or recently had a heart attack
- have an irregular heart rhythm or heartbeat (QT prolongation, heart arrhythmia)
- are pregnant or plan to become pregnant. INGREZZA or INGREZZA SPRINKLE may harm your unborn baby.
- are breastfeeding or plan to breastfeed. It is not known if INGREZZA or INGREZZA SPRINKLE passes into your breast milk. Do not breastfeed during treatment with INGREZZA or INGREZZA SPRINKLE and for 5 days after the final dose. Talk to your healthcare provider about the best way to feed your baby during treatment with INGREZZA or INGREZZA SPRINKLE.

Tell your healthcare provider about all the medicines you take, including prescription and over-the-counter medicines, vitamins and herbal supplements. Make sure you tell all of your healthcare providers that you are taking INGREZZA or INGREZZA SPRINKLE. Taking INGREZZA or INGREZZA SPRINKLE with certain other medicines may cause serious side effects and may affect the way that INGREZZA or INGREZZA SPRINKLE works. Especially tell your healthcare provider if you:

- take or have taken a monoamine oxidase inhibitor (MAOI) medicine. You should not take INGREZZA or INGREZZA SPRINKLE if you are taking, or have stopped taking, a MAOI within the last 14 days. Ask your healthcare provider if you are not sure if you take a MAOI.
- take digoxin

Do not start any new medicines during treatment with INGREZZA or INGREZZA SPRINKLE without talking to your healthcare provider first.

How should I take INGREZZA or INGREZZA SPRINKLE?

- Take INGREZZA or INGREZZA SPRINKLE exactly as your healthcare provider tells you to.
- Your healthcare provider may change your dose of INGREZZA or INGREZZA SPRINKLE during treatment.
- Take INGREZZA or INGREZZA SPRINKLE 1 time each day.
- Take INGREZZA or INGREZZA SPRINKLE with or without food.
- If you take INGREZZA, swallow the capsule
- If you take INGREZZA SPRINKLE:
  ○ You may open the capsule and sprinkle the contents (granules) over a small amount (1 tablespoonful) of soft food such as applesauce, yogurt, or pudding before taking INGREZZA SPRINKLE.
  ○ You may also swallow the capsule whole with water.
  ○ Do not add the granules to milk or water.
  ○ Do not crush or chew INGREZZA SPRINKLE.
  ○ See the detailed Instructions for Use on how to take a dose of INGREZZA SPRINKLE.
- If you take too much INGREZZA or INGREZZA SPRINKLE, call your healthcare provider or Poison Help line at 1-800-222-1222, or go to the nearest hospital emergency room right away.

What should I avoid while taking INGREZZA or INGREZZA SPRINKLE?
Do not drive a car or operate dangerous machinery until you know how INGREZZA or INGREZZA SPRINKLE affects you because INGREZZA or INGREZZA SPRINKLE can cause sleepiness and tiredness that could cause slow reaction times. Drinking alcohol and taking other medicines that may also cause sleepiness during treatment with INGREZZA or INGREZZA SPRINKLE may increase any sleepiness caused by INGREZZA or INGREZZA SPRINKLE.

What are the possible side effects of INGREZZA or INGREZZA SPRINKLE?
INGREZZA or INGREZZA SPRINKLE can cause serious side effects, including:

- See “What is the most important information I should know about INGREZZA or INGREZZA SPRINKLE?”
- Allergic Reactions. Allergic reactions, including an allergic reaction that causes sudden swelling called angioedema, can happen after taking the first dose or after many doses of INGREZZA or INGREZZA SPRINKLE. Signs and symptoms of allergic reactions and angioedema include:
  ○ trouble breathing or shortness of breath
  ○ swelling of your face, lips, eyelids, tongue, or throat, or other areas of your skin
  ○ trouble with swallowing
  ○ rash, including raised, itchy red areas on your skin (hives)
  Swelling in the throat can be life-threatening and can lead to death. Stop taking INGREZZA or INGREZZA SPRINKLE right away and go to the nearest emergency room right away if you develop these signs and symptoms of allergic reactions and angioedema.
- Sleepiness and tiredness that could cause slow reaction times (somnolence and sedation). See “What should I avoid while taking INGREZZA or INGREZZA SPRINKLE?”
- Heart rhythm problems (QT prolongation). INGREZZA or INGREZZA SPRINKLE may cause a heart rhythm problem known as QT prolongation. You have a higher chance of getting QT prolongation if you also take certain other medicines during treatment with INGREZZA or INGREZZA SPRINKLE. Tell your healthcare provider right away if you develop any signs or symptoms of QT prolongation, including:

◦ fast, slow, or irregular heartbeat (heart palpitations)

◦ shortness of breath

◦ dizziness or lightheadedness

◦ fainting or feeling like you are going to faint.

- Neuroleptic Malignant Syndrome (NMS). NMS is a serious condition that can lead to death. Call a healthcare provider right away or go to the nearest emergency room if you develop these signs and symptoms that do not have another obvious cause:

◦ high fever

◦ stiff muscles

◦ problems thinking

◦ irregular pulse or blood pressure

◦ increased sweating

◦ very fast or uneven heartbeat

- Parkinson-like symptoms. Tell your healthcare provider if you develop any Parkinson-like symptoms during treatment with INGREZZA or INGREZZA SPRINKLE, including:

◦ body stiffness

◦ drooling

◦ trouble moving or walking

◦ trouble keeping your balance

◦ shaking (tremors)

◦ falls

The most common side effect of INGREZZA or INGREZZA SPRINKLE in people with tardive dyskinesia is sleepiness and tiredness that could cause slow reaction times.
The most common side effects of INGREZZA or INGREZZA SPRINKLE in people with chorea associated with Huntington’s disease include sleepiness and tiredness that could cause slow reaction times, raised itchy red areas on your skin (hives), rash, and trouble getting to sleep or staying asleep.
Your doctor may change your dose, temporarily stop, or permanently stop treatment with INGREZZA or INGREZZA SPRINKLE if you develop certain side effects.
These are not all of the possible side effects of INGREZZA or INGREZZA SPRINKLE.
Call your doctor for medical advice about side effects. You may report side effects to FDA at 1-800-FDA-1088.

How should I store INGREZZA or INGREZZA SPRINKLE?

- Store INGREZZA at 59°F to 86°F (15°C to 30°C).
- Store INGREZZA SPRINKLE between 68°F to 77°F (20°C to 25°C).
- Keep the bottle tightly closed to protect INGREZZA SPRINKLE from moisture.
- INGREZZA SPRINKLE granules added to soft food can be stored for up to 2 hours at room temperature between 68°F to 77°F (20°C to 25°C). After 2 hours, throw away any unused portion.
- Keep INGREZZA, INGREZZA SPRINKLE and all medicines out of the reach of children.

General information about the safe and effective use of INGREZZA or INGREZZA SPRINKLE.
Medicines are sometimes prescribed for purposes other than those listed in the Medication Guide. Do not use INGREZZA or INGREZZA SPRINKLE for a condition for which it was not prescribed. Do not give INGREZZA or INGREZZA SPRINKLE to other people, even if they have the same symptoms that you have. It may harm them. You can ask your pharmacist or healthcare provider for information about INGREZZA or INGREZZA SPRINKLE that is written for healthcare professionals.

What are the ingredients in INGREZZA or INGREZZA SPRINKLE?
Active ingredient: valbenazine
INGREZZA Inactive ingredients: hypromellose, isomalt, magnesium stearate, pregelatinized starch, and silicified microcrystalline cellulose. The capsule shells contain candurin silver fine, FD&C Blue#1, FD&C Red#40, and gelatin.
INGREZZA SPRINKLE inactive ingredients: silicified microcrystalline cellulose, isomalt, pregelatinized maize starch, hypromellose, magnesium stearate, polyvinyl alcohol, titanium dioxide, polyethylene glycol, and talc. The hard gelatin capsule shells contain gelatin and candurin silver fine.

Distributed by: Neurocrine Biosciences, Inc., San Diego, CA 92130, U.S.A.
For more information, go to www.INGREZZA.com or call 84-INGREZZA (844-647-3992).

This Medication Guide has been approved by the U.S. Food and Drug Administration Revised: 4/2024

INSTRUCTIONS FOR USE
INGREZZA® SPRINKLE (in greh' zah spring kuhl)
(valbenazine)
capsules

This Instructions for Use contains information on how to take INGREZZA SPRINKLE.
Important Information You Need to Know Before Taking INGREZZA SPRINKLE

- You can open the INGREZZA SPRINKLE capsule and sprinkle the contents (granules) on soft food such as applesauce, yogurt, or pudding before you take it.
- You can also swallow the INGREZZA SPRINKLE capsule whole with water with or without food.
- Do not add the granules to milk or water before you take INGREZZA SPRINKLE.
- Do not take INGREZZA SPRINKLE through a nasogastric tube (NG Tube), gastrostomy tube (G Tube), or other feeding tube because it may clog the tube.
- Do not crush or chew INGREZZA SPRINKLE.
- Check to make sure that you have received your prescribed strength of INGREZZA SPRINKLE before taking your dose.
- Check the expiration date on the INGREZZA SPRINKLE bottle. Do not take INGREZZA SPRINKLE if it is expired. Call your healthcare provider or pharmacist if your medicine is expired.

Preparing to Take INGREZZA SPRINKLE
Step 1
Gather your supplies.
You will need (see Figure A):

- The prescribed number of INGREZZA SPRINKLE capsules.
- Soft food such as applesauce, yogurt, or pudding. You will need 1 tablespoonful of soft food.
- A clean tablespoon.
- A clean container such as a small cup or bowl.

Figure A.

Step 2
Wash and dry your hands (see Figure B).

Figure B.

Step 3
Place the following items on a clean flat surface:

- A tablespoon.
- A container of soft food such as applesauce, yogurt, or pudding.

- The number of capsules you will need for your prescribed dose.
- A small cup or bowl.

Step 4
Place 1 tablespoonful of soft food into a small cup or bowl (see Figure C).

Figure C.

Step 5
Opening the INGREZZA SPRINKLE capsule and sprinkling the granules on the soft food

- Hold the INGREZZA SPRINKLE capsule carefully over the soft food (see Figure D).
- Gently pull the INGREZZA SPRINKLE capsule apart, empty the capsule contents (granules) onto the soft food (see Figure E).

Figure D.
Figure E.

- Check the capsule to make sure that you did not miss any granules.
- Tap the capsule to remove any remaining granules.
- Stir the granules into the soft food with the tablespoon (see Figure F).

Do not crush the granules while stirring them into the soft food.

Figure F.

Step 6
Taking the soft food and INGREZZA SPRINKLE mixture

- Eat all of the food right away after adding the granules.
- Do not chew the granules.
- After eating all of the INGREZZA SPRINKLE soft food mixture, drink a glass of water (about 8 ounces or 240 mL) to make sure that all of the medicine is swallowed.
- If you need to, you can store the mixture for up to 2 hours at room temperature between 68°F to 77°F (20°C to 25°C). After 2 hours, throw away any unused portion of the mixture.

Step 7
Cleaning Up and Disposing of INGREZZA SPRINKLE

- Throw away (dispose of) the empty capsule shells in your household trash (see Figure G).
- Wash your hands and all the items used to prepare and take INGREZZA SPRINKLE.

Ask your pharmacist how to dispose of expired medicines or medicines you no longer use.

Figure G.

Storing INGREZZA SPRINKLE

- Store INGREZZA SPRINKLE between 68°F to 77°F (20°C to 25°C).
- Protect INGREZZA SPRINKLE from moisture to help keep the capsules dry.
- INGREZZA SPRINKLE granules added to soft food can be stored for up 2 hours at room temperature between 68°F to 77°F (20°C to 25°C). After 2 hours, throw away any unused portion.

Keep INGREZZA SPRINKLE and all medicines out of the reach of children.

Distributed by: Neurocrine Biosciences, Inc., San Diego, CA 92130
For more information, go to www.INGREZZA.com or call 84-INGREZZA (844-647-3992).

This Instructions for Use has been approved by the U.S. Food and Drug Administration.

Approved: 4/2024

PACKAGE LABEL

PRINCIPAL DISPLAY PANEL

NDC 70370-2040-1
INGREZZA
(valbenazine) capsules
40 mg
30 Capsules
Rx Only

PACKAGE LABEL

PRINCIPAL DISPLAY PANEL

NDC 70370-1060-1
INGREZZA
(valbenazine) capsules
60 mg
30 Capsules
Rx Only

PACKAGE LABEL

PRINCIPAL DISPLAY PANEL

NDC 70370-1080-1
INGREZZA
(valbenazine) capsules
80 mg
30 Capsules
Rx Only

PACKAGE LABEL

PRINCIPAL DISPLAY PANEL

NDC 70370-2048-6
INGREZZA
(valbenazine) capsules
7 x 40 mg / 21 x 80 mg capsules
28-day Initiation Pack
Rx Only

PACKAGE LABEL

PRINCIPAL DISPLAY PANEL

NDC 70370-2046-1
INGREZZA
(valbenazine) capsules
14 x 40 mg / 14 x 60 mg capsules
28-day Initiation Pack
Rx Only

PACKAGE LABEL

PRINCIPAL DISPLAY PANEL

NDC 70370-4040-1
INGREZZA SPRINKLE
(valbenazine) capsules
40 mg
30 capsules
Rx Only

PACKAGE LABEL

PRINCIPAL DISPLAY PANEL

NDC 70370-4060-1
INGREZZA SPRINKLE
(valbenazine) capsules
60 mg
30 capsules
Rx Only

PACKAGE LABEL

PRINCIPAL DISPLAY PANEL

NDC 70370-4080-1
INGREZZA SPRINKLE
(valbenazine) capsules
80 mg
30 capsules
Rx Only